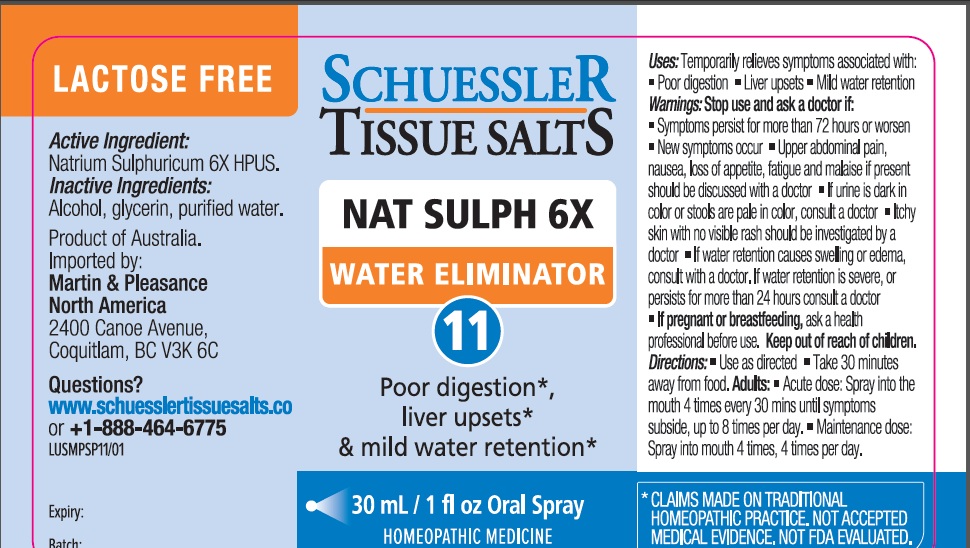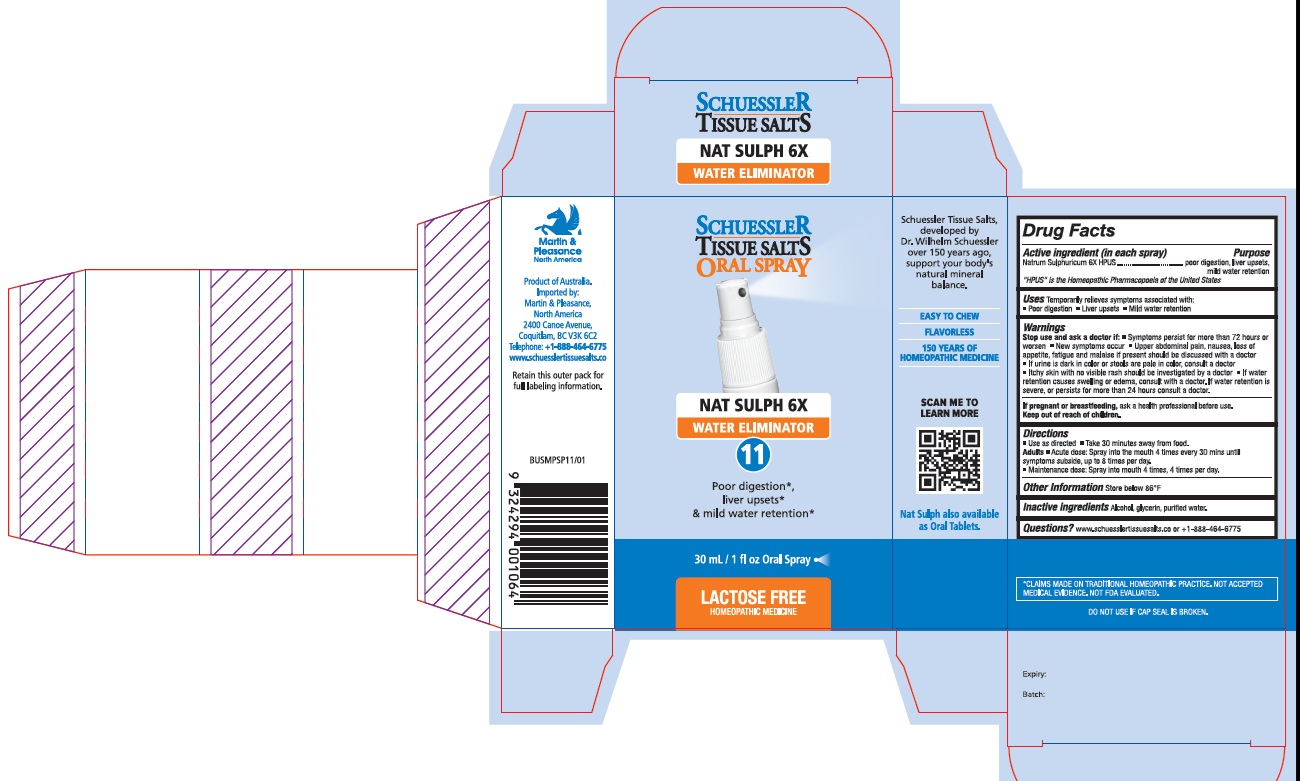 DRUG LABEL: Schuessler Tissue Salts Nat Sulph Water Eliminator 11
NDC: 84999-011 | Form: SPRAY
Manufacturer: Martin & Pleasance Pty Ltd
Category: homeopathic | Type: HUMAN OTC DRUG LABEL
Date: 20250707

ACTIVE INGREDIENTS: SODIUM SULFATE ANHYDROUS 6 [hp_X]/30 mL
INACTIVE INGREDIENTS: ALCOHOL; GLYCERIN; WATER

Active ingredient (in each spray) Purpose

Natrum Sulphuricum 6X HPUS poor digestion, liver upsets, mild water retention

Uses

Temporarily relieves symptoms associated with:

• Poor digestion

• Liver upsets

• Mild water retention

Warnings

Stop use and ask a doctor if:

- Symptoms persist for more than 72 hours or worsen
- New symptoms occur
- Upper abdominal pain, nausea, loss of appetite, fatigue and malaise if present should be discussed with a doctor
- If urine is dark in color or stools are pale in color, consult a doctor
- Itchy skin with no visible rash should be investigated by a doctor
- If water retention causes swelling or edema, consult with a doctor. If water retention is severe, or persists for more than 24 hours consult a doctor.

If pregnant or breastfeeding, ask a health professional before use. Keep out of reach of children.

Directions

- Use as directed
- Take 30 minutes away from food.

Adults

- Acute dose: Spray into the mouth 4 times every 30 mins until symptoms subside, up to 8 times per day.
- Maintenance dose: Spray into mouth 4 times, 4 times per day.

Other Information

Store below 86°F

Inactive Ingredients

Alcohol, Glycerin, Purified Water

Questions?www.schuesslertissuesalts.co or + 1-888-464-6775